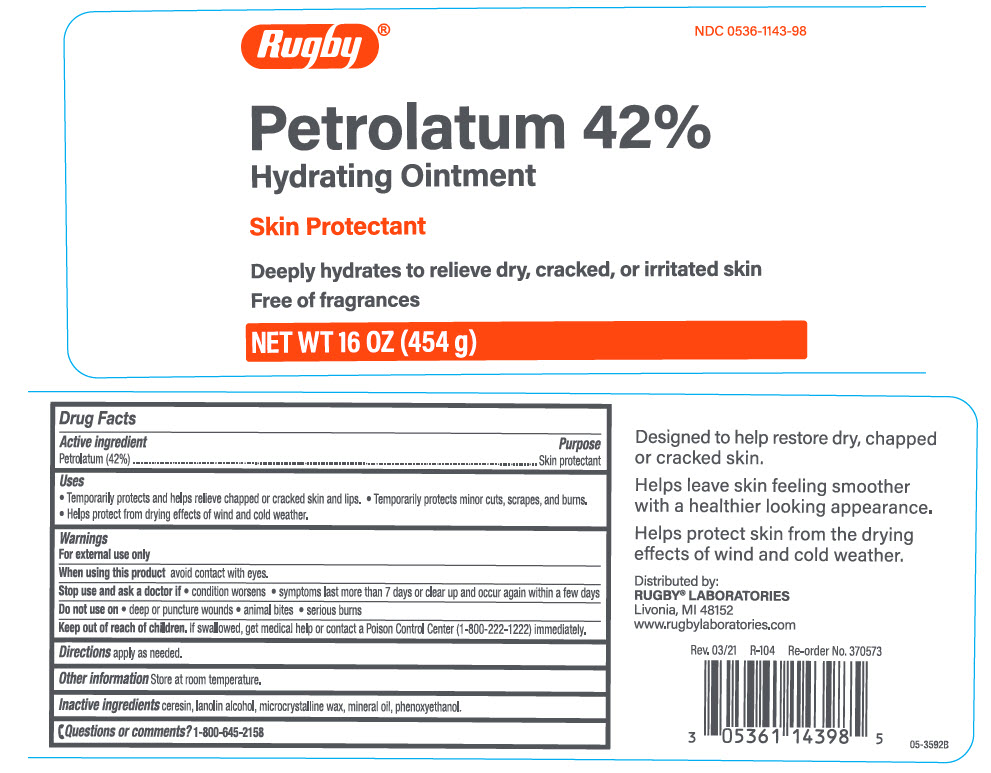 DRUG LABEL: Rugby Petrolatum Hydrating
NDC: 0536-1143 | Form: OINTMENT
Manufacturer: Rugby Laboratories
Category: otc | Type: HUMAN OTC DRUG LABEL
Date: 20240212

ACTIVE INGREDIENTS: Petrolatum 420 mg/1 g
INACTIVE INGREDIENTS: Ceresin; LANOLIN ALCOHOLS; Microcrystalline Wax; Mineral Oil; Phenoxyethanol

Rugby® Petrolatum 42% Hydrating Ointment
Skin Protectant

Drug Facts

Active ingredient

Petrolatum (42%)

Purpose

Skin protectant

Uses

- Temporarily protects and helps relieve chapped or cracked skin and lips.
- Temporarily protects minor cuts, scrapes, and burns.
- Helps protect from drying effects of wind and cold weather.

Warnings

For external use only

When using this product avoid contact with eyes.

Stop use and ask a doctor if

- condition worsens
- symptoms last more than 7 days or clear up and occur again within a few days

Do not use

- deep or puncture wounds
- animal bites
- serious burns

Keep out of reach of children. If swallowed, get medical help or contact a Poison Control Center (1-800-222-1222) immediately.

Directions

apply as needed.

Other information

Store at room temperature.

Inactive ingredients

ceresin, lanolin alcohol, microcrystalline wax, mineral oil, phenoxyethanol.

Questions or comments?

1-800-645-2158

Distributed by:
RUGBY® LABORATORIES
Livonia, MI 48152

PRINCIPAL DISPLAY PANEL - 454 g Jar Label

Rugby®
NDC 0536-1143-98

Petrolatum 42%
Hydrating Ointment

Skin Protectant

Deeply hydrates to relieve dry, cracked, or irritated skin

Free of fragrances

NET WT 16 OZ (454 g)